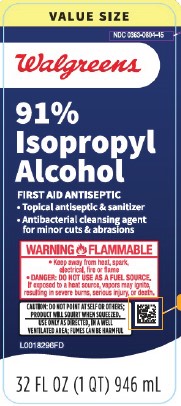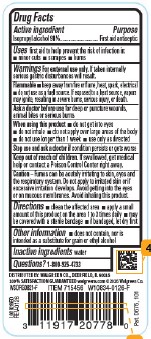 DRUG LABEL: Isopropyl Alcohol
NDC: 0363-0804 | Form: LIQUID
Manufacturer: Walgreens Co.
Category: otc | Type: HUMAN OTC DRUG LABEL
Date: 20260205

ACTIVE INGREDIENTS: ISOPROPYL ALCOHOL 91 mL/100 mL
INACTIVE INGREDIENTS: WATER

Walgreens 804.003/804AA
91% Isopropyl Alcohol

Active ingredient

Isopropyl alcohol 91%

Purpose

First aid antiseptic

Uses

first aid to help prevent the risk of infection in:

- minor cuts
- scrapes
- burns

Warnings

For external use only. If taken internally serious gastric disturbances will result.

Flammable

- Keep away from fire or flame, heat, spark, electrical
- do not use as a fuel source. If exposed to a heat source, vapors may ignite, resulting in severe burns, serious injury, or death.

Ask a doctor before use

for deep wounds, animal bites or serious burns

When using this product

- do not get into eyes
- do not inhale
- do not apply over large areas of the body
- do not use longer than 1 week
- use only as directed

Stop use and ask a doctor if

condition persists or gets worse

Keep out of reach of children.

If swallowed, get medical help or contact a Poison Control Center right away.

Cautions

Fumes can be acutely irritating to skin, eyes and respiratory system. Do not apply to irriated skin or if excessive irritation develops. Avoid getting into the eyes or on mucous membranes. Avoid inhaling this product.

Directions

- clean the affected area
- apply a small amount of this product on the area 1 to 3 times daily
- may be covered with a sterile bandage
- if bandaged, let dry first

Other information

- does not contain, nor is intended as a substitute for grain or ethyl alcohol

Inactive ingredient

water

Questions?

1-800-925-4733

ADVERSE REACTION

DISTRIBUTED BY: WALGREEN CO., DEERFIELD, IL 60015

100% SATISFACTION GUARANTEED walgreens.com ©2026 Walgreen Co.

Pat. D675, 101

Principal display panel

VALUE SIZE

NDC 0363-0804-45

Walgreens

91% Isopropyl Alcohol

FIRST AID ANTISEPTIC

- Topical antiseptic & sanitizer
- Antibacterical cleansing agent for minor cuts & abrasions

WARNING FLAMMABLE

- Keep away from heat, spark, electrical, fire or flame
- DANGER: DO NOT USE AS A FUEL SOURCE.

If exposed to a heat source, vapors may ignite, resulting in severe burns, serious injury, or death.

CAUTION: DO NOT POINT AT SELF OR OTHERS; PRODUCT WILL SQUIRT WHEN SQUEEZED

USE ONLY AS DIRECTED, IN A WELL-VENTILATED AREA; FUMES CAN BE HARMFUL

32 FL OZ (1 QT) 946 mL